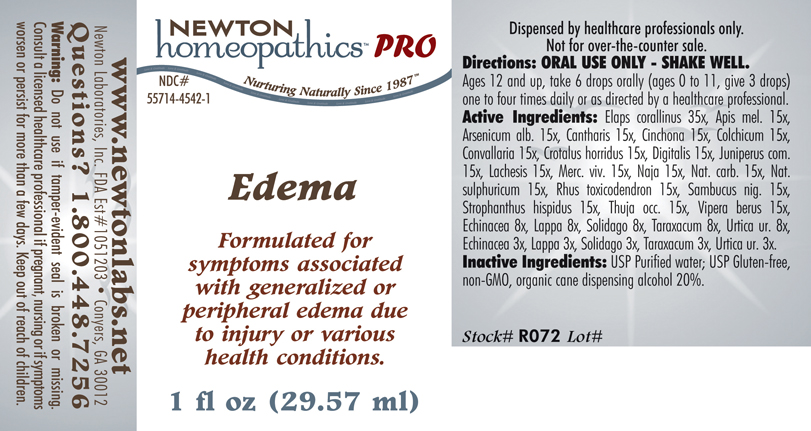 DRUG LABEL: Edema 
NDC: 55714-4542 | Form: LIQUID
Manufacturer: Newton Laboratories, Inc.
Category: homeopathic | Type: HUMAN PRESCRIPTION DRUG LABEL
Date: 20110601

ACTIVE INGREDIENTS: Micrurus Corallinus Venom 35 [hp_X]/1 mL; Apis Mellifera 15 [hp_X]/1 mL; Arsenic Trioxide 15 [hp_X]/1 mL; Lytta Vesicatoria 15 [hp_X]/1 mL; Cinchona Officinalis Bark 15 [hp_X]/1 mL; Colchicum Autumnale Bulb 15 [hp_X]/1 mL; Convallaria Majalis 15 [hp_X]/1 mL; Crotalus Horridus Horridus Venom 15 [hp_X]/1 mL; Digitalis 15 [hp_X]/1 mL; Juniperus Communis Fruit 15 [hp_X]/1 mL; Lachesis Muta Venom 15 [hp_X]/1 mL; Mercury 15 [hp_X]/1 mL; Naja Naja Venom 15 [hp_X]/1 mL; Sodium Carbonate 15 [hp_X]/1 mL; Sodium Sulfate 15 [hp_X]/1 mL; Toxicodendron Pubescens Leaf 15 [hp_X]/1 mL; Sambucus Nigra Flowering Top 15 [hp_X]/1 mL; Strophanthus Hispidus Seed 15 [hp_X]/1 mL; Thuja Occidentalis Leafy Twig 15 [hp_X]/1 mL; Vipera Berus Venom 15 [hp_X]/1 mL; Echinacea, Unspecified 8 [hp_X]/1 mL; Arctium Lappa Root 8 [hp_X]/1 mL; Solidago Virgaurea Flowering Top 8 [hp_X]/1 mL; Taraxacum Officinale 8 [hp_X]/1 mL; Urtica Urens 8 [hp_X]/1 mL
INACTIVE INGREDIENTS: Alcohol

Edema

INDICATIONS & USAGE SECTION

Edema Formulated for symptoms associated with generalized or peripheral edema due to injury or various health conditions.

DOSAGE & ADMINISTRATION SECTION

Directions: ORAL USE ONLY - SHAKE WELL. Ages 12 and up, take 6 drops orally (ages 0 to 11, give 3 drops) one to four times daily or as directed by a healthcare professional.

ACTIVE INGREDIENT SECTION

Elaps corallinus 35x, Apis mel.15x, Arsenicum alb. 15x, Cantharis 15x, Cinchona 15x, Colchicum 15x, Convallaria 15x, Crotalus horridus 15x, Digitalis 15x, Juniperus com 15x, Lachesis 15x, Merc. viv. 15x, Naja 15x, Nat. carb. 15x, Nat. sulphuricum 15x, Rhus toxicodendron 15x, Sambucus nig. 15x, Strophanthus hispidus 15x, Thuja occ. 15x, Vipera berus 15x, Echinacea 8x, Lappa 8x, Solidago 8x, Taraxacum 8x, Urtica ur. 8x, Echinacea 3x, Lappa 3x, Solidago 3x, Taraxacum 3x, Urtica ur. 3x.

PURPOSE SECTION

Formulated for symptoms associated with generalized or peripheral edema due to injury or various health conditions.

INACTIVE INGREDIENT SECTION

Inactive Ingredients: USP Purified Water; USP Gluten-free, non-GMO, organic cane dispensing alcohol 20%.

QUESTIONS? SECTION

www.newtonlabs.net Newton Laboratories, Inc. FDA Est # 1051203 - Conyers, GA 30012
Questions? 1.800.448.7256

WARNINGS SECTION

Warning: Do not use if tamper - evident seal is broken or missing. Consult a licensed healthcare professional if pregnant, nursing or if symptoms worsen or persist for more than a few days. Keep out of reach of children.

PREGNANCY OR BREAST FEEDING SECTION

Consult a licensed healthcare professional if pregnant or nursing or if symptoms worsen or persist for more than a few days.

KEEP OUT OF REACH OF CHILDREN SECTION

Keep out of reach of children.